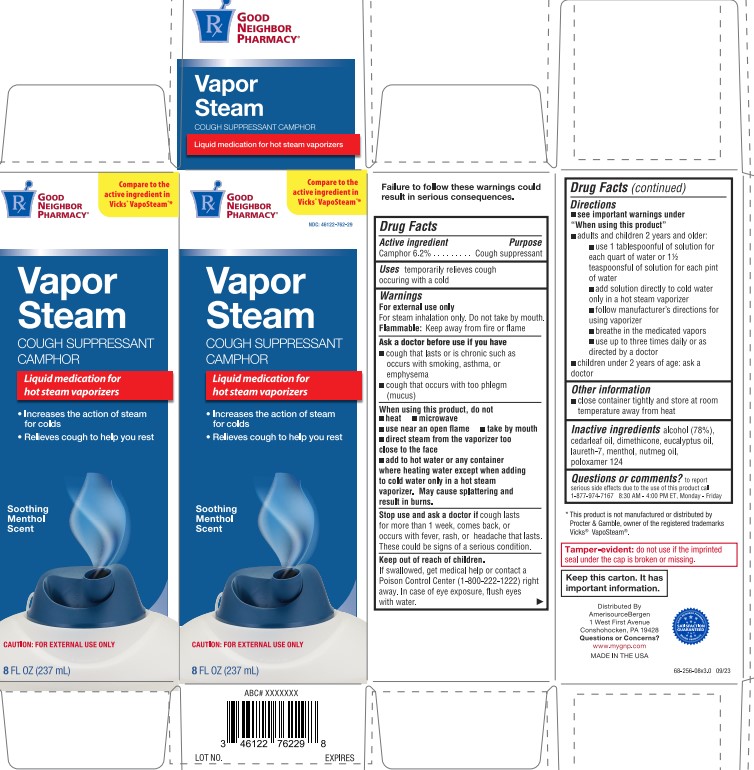 DRUG LABEL: GNP Vapor Steam camphor (synthetic)
NDC: 46122-762 | Form: LIQUID
Manufacturer: AmerisourceBergen
Category: otc | Type: HUMAN OTC DRUG LABEL
Date: 20260126

ACTIVE INGREDIENTS: CAMPHOR (SYNTHETIC) 0.062 g/1 mL
INACTIVE INGREDIENTS: NUTMEG OIL; POLOXAMER 124; LAURETH-7; DIMETHICONE; MENTHOL; CEDAR LEAF OIL; ALCOHOL; EUCALYPTUS OIL

GNP Vapor Steam

Drug Facts

Active ingredient

Camphor 6.2%

Purpose

Cough suppressant

Use

temporarily relieves cough ocurring with a cold

Warnings

For external use only.
Flammable: Keep away from fire or flame.
For steam inhalation only.

Ask a doctor before use if you have

- a cough that lasts or is chronic such as occurs with smoking, asthma, or emphysema
- cough that ocurs with too much phlegm (mucus)

When using this product, do not

- heat
- microwave
- use near an open flame
- take by mouth
- direct steam from the vaporizer too close to the face
- add to hot water or any container where heating water except when adding to cold water only in a hot steam vaporizer. May cause splattering and result in burns.

Stop use and ask a doctor if

cough lasts more than 7 days, comes back, or occurs with fever, rash, or headache that lasts. These could be signs of a serious condition.

Keep out of reach of children.

If swallowed, get medical help or contact a Poison Control Center right away. In case of eye exposure, flush with water.

If pregnant or breast-feeding,

ask a health professional before use.

Directions

- see important warnings under "When using this product"
- adults & children 2 years & over:
- use 1 tablespoon of solution for each quart of water or 1½ teaspoonful of solution for each pint of water
- add solution directly to cold water only in a hot steam vaporizer
- follow manufacturer's directions for using vaporizer
- breathe in the medicated vapors
- use up to three times daily or as directed by a doctor
- children under 2 years: ask a doctor

Other information

close container tightly and store at room temperature away from heat

Inactive ingredients

alcohol (78%), cedarleaf oil, dimethicone, eucalyptus oil, laureth-7, menthol, nutmeg oil, poloxamer 124

Tamper-evident: do not use if the imprinted seal under the cap is broken or missing.

Keep this carton. It has important information.

PRINCIPAL DISPLAY PANEL - 8oz

CAUTION: NOT FOR INTERNAL USE

NDC 46122-762-29

GNP

Vapor Steam

Liquid Medication For Hot Steam Vaporizers

Increases the action of steam for colds

Relieves cough to help you rest

Soothing Menthol Scent

Compare Vicks® Vapo Steam active ingredient*

Caution: for external use only

8 fl oz (237 mL)